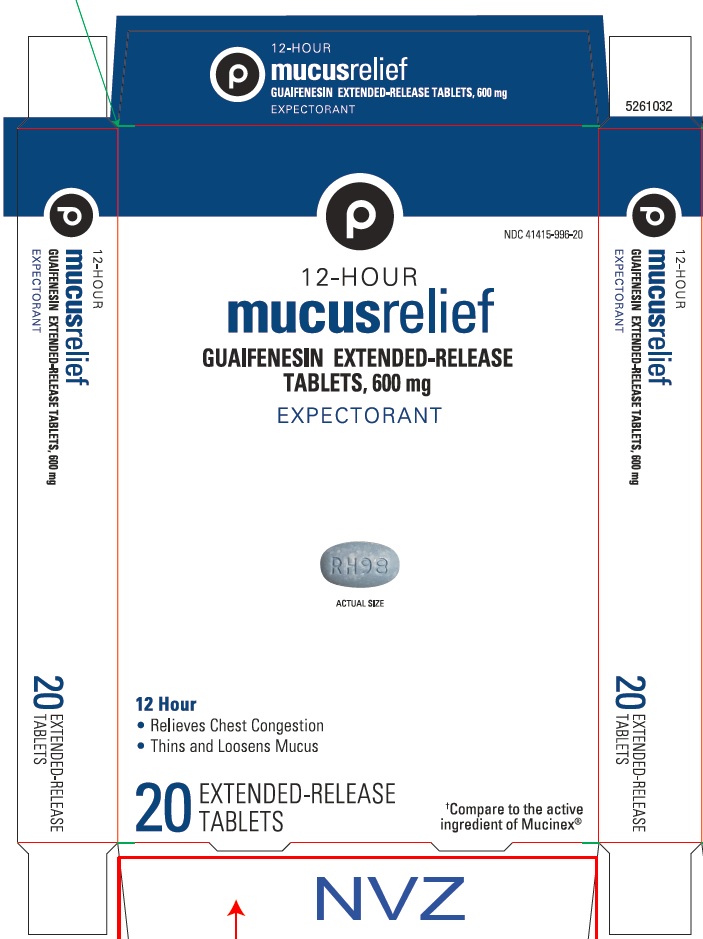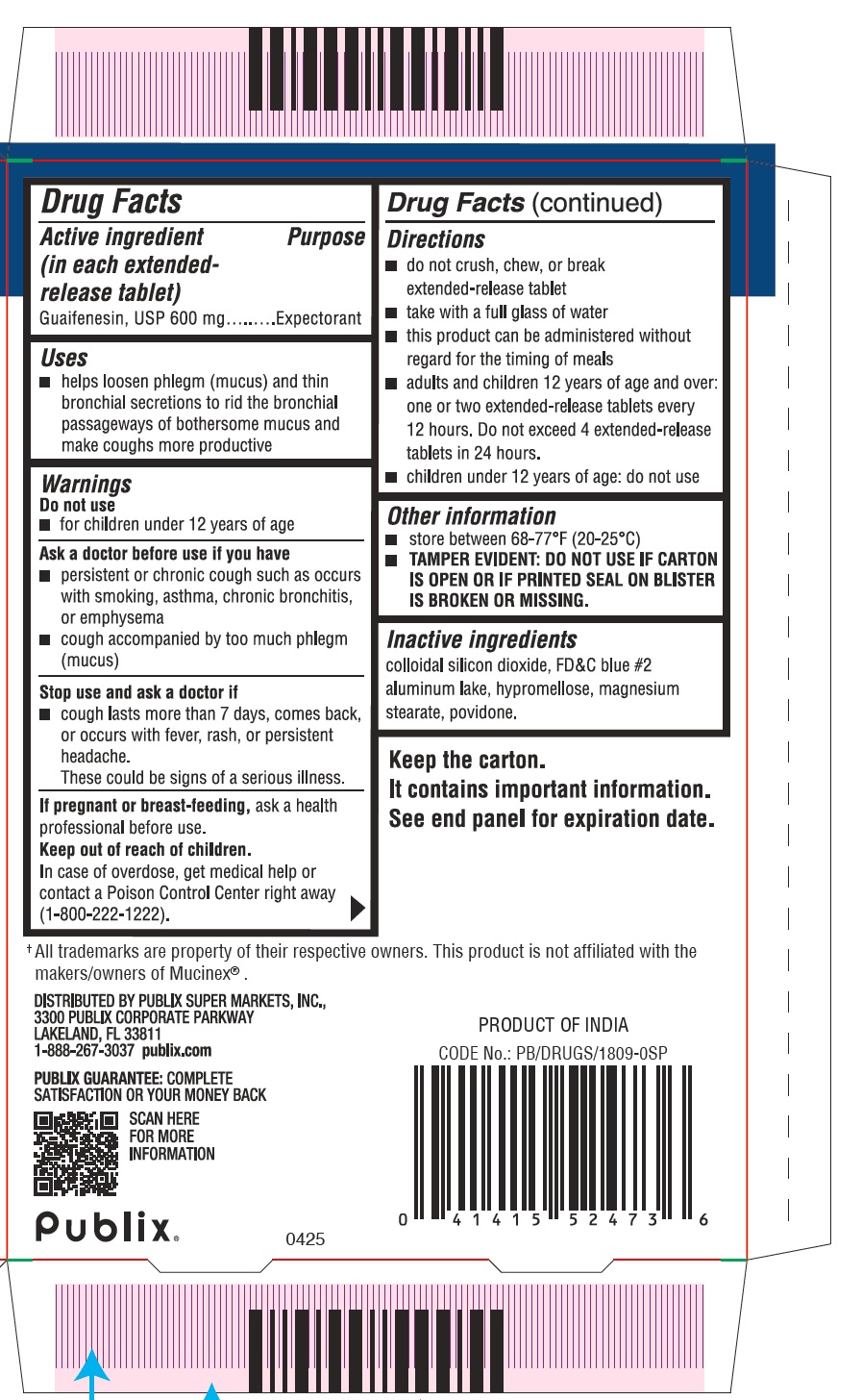 DRUG LABEL: GUAIFENESIN
NDC: 41415-996 | Form: TABLET, EXTENDED RELEASE
Manufacturer: Publix Super Markets, Inc
Category: otc | Type: HUMAN OTC DRUG LABEL
Date: 20250520

ACTIVE INGREDIENTS: GUAIFENESIN 600 mg/1 1
INACTIVE INGREDIENTS: HYPROMELLOSE, UNSPECIFIED; MAGNESIUM STEARATE; SILICON DIOXIDE; FD&C BLUE NO. 2; POVIDONE, UNSPECIFIED

GUAIFENESIN EXTENDED-RELEASE TABLETS, 600 mg

Drug Facts

Active ingredient (in each extended-release tablet)

Guaifenesin, USP 600 mg

Purpose

Expectorant

Uses

- helps loosen phlegm (mucus) and thin bronchial secretions to rid the bronchial passageways of bothersome mucus and make coughs more productive

Warnings

Do not use

- for children under 12 years of age

Ask a doctor before use if you have

- persistent or chronic cough such as occurs with smoking, asthma, chronic bronchitis, or emphysema
- cough accompanied by too much phlegm (mucus)

Stop use and ask a doctor if

- cough lasts more than 7 days, comes back, or occurs with fever, rash, or persistent headache.
  These could be signs of a serious illness.

PREGNANCY OR BREAST FEEDING

If pregnant or breast-feeding,ask a health professional before use.

Keep out of reach of children.

In case of overdose, get medical help or contact a Poison Control Center right away (1-800-222-1222).

Directions

- do not crush, chew, or break extended-release tablet
- take with a full glass of water
- this product can be administered without regard for the timing of meals
- adults and children 12 years of age and over: one or two extended-release tablets every 12 hours. Do not exceed 4 extended-release tablets in 24 hours.
- children under 12 years of age: do not use

Other information

- store between 68-77°F (20-25°C)
- TAMPER EVIDENT: DO NOT USE IF CARTON IS OPEN OR IF PRINTED SEAL ON BLISTER IS BROKEN OR MISSING.

Inactive ingredients

colloidal silicon dioxide, FD&C blue #2 aluminum lake, hypromellose, magnesium stearate, povidone.

DISTRIBUTED BY PUBLIX SUPER MARKETS, INC.,
3300 PUBLIX CORPORATE PARKWAY
LAKELAND, FL 33811

PRINCIPAL DISPLAY PANEL - 20 extended-release Tablets Blister Pack Carton

NDC 41415-996-20

12-HOUR
mucus relief

GUAIFENESIN EXTENDED-RELEASE
TABLETS, 600 mg

EXPECTORANT

12 Hour

- Relieves Chest Congestion
- Thins and Loosens Mucus

20
EXTENDED-RELEASE
TABLETS

†Compare to the active
ingredient of Mucinex®